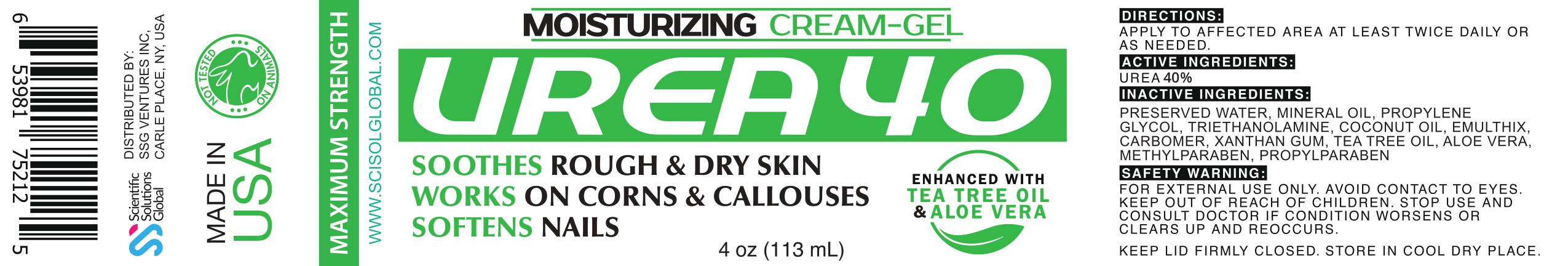 DRUG LABEL: Urea 40
NDC: 81376-211 | Form: GEL
Manufacturer: SSG Ventures Inc
Category: otc | Type: HUMAN OTC DRUG LABEL
Date: 20210407

ACTIVE INGREDIENTS: UREA 4 g/10 mL
INACTIVE INGREDIENTS: METHYLPARABEN; PROPYLPARABEN; ALOE VERA LEAF; CARBOMER HOMOPOLYMER, UNSPECIFIED TYPE; XANTHAN GUM; MINERAL OIL; COCONUT OIL; WATER; TROLAMINE; TEA TREE OIL; PROPYLENE GLYCOL

Urea 40

PACKAGE LABEL

ACTIVE INGREDIENTS:

UREA 40%

PURPOSE

SOOTHES ROUGH & DRY SKIN

HEALS CORNS & CALLOUSES

INDICATIONS AND USAGE

SOOTHES ROUGH & DRY SKIN

SAFE HANDLING WARNING

FOR EXTERNAL USE ONLY. AVOID CONTACT TO EYES.

KEEP OUT OF REACH OF CHILDREN. STOP USE AND CONSULT DOCTOR IF CONDITION WORSENS OR CLEARS UP AND REOCCURS.

KEEP LID FIRMLY CLOSED. STORE IN COOL DRY PLACE.

KEEP OUT OF REACH OF CHILDREN.

INSTRUCTIONS FOR USE

APPLY TO AFFECTED AREA AT LEAST TWICE DAILY OR AS NEEDED.USE CONTINUOUSLY FOR 2-3 WEEKS FOR OPTIMAL RESULTS.

INACTIVE INGREDIENT

PRESERVED WATER, MINERAL OIL, PROPYLENE GLYCOL, TRIETHANOLAMINE, COCONUT OIL, EMULTHIX, CARBOMER, XANTHAM GUM, TEA TREE OIL, ALOE VERA, METHYLPARABEN, PROPYLPARABEN

STORAGE AND HANDLING

KEEP LID FIRMLY CLOSED. STORE IN COOL DRY PLACE.

OTHER SAFETY INFORMATION

ENHANCED WITH TEA TREE OIL & ALOE VERA

DOSAGE AND ADMINISTRATION

APPLY TO AFFECTED AREA AT LEAST TWICE DAILY OR AS NEEDED.USE CONTINUOUSLY FOR 2-3 WEEKS FOR OPTIMAL RESULTS.

WARNINGS

FOR EXTERNAL USE ONLY. AVOID CONTACT TO EYES. STOP USE AND CONSULT DOCTOR IF CONDITION WORSENS OR CLEARS UP AND REOCCURS.